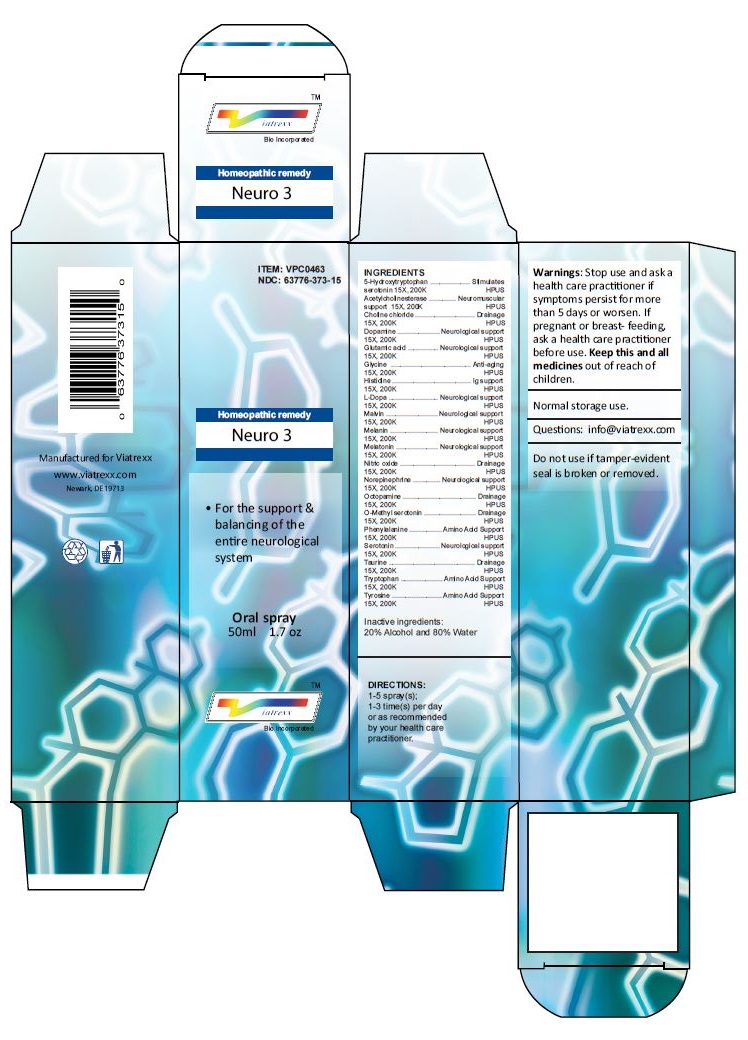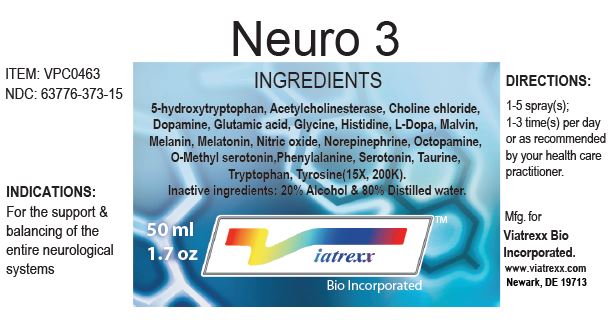 DRUG LABEL: Neuro 3
NDC: 63776-373 | Form: SPRAY
Manufacturer: VIATREXX BIO INCORPORATED
Category: homeopathic | Type: HUMAN OTC DRUG LABEL
Date: 20230110

ACTIVE INGREDIENTS: OXITRIPTAN 200 [kp_C]/1 mL; ACETYLCHOLINESTERASE HUMAN 200 [kp_C]/1 mL; CHOLINE CHLORIDE 200 [kp_C]/1 mL; DOPAMINE 200 [kp_C]/1 mL; GLUTAMIC ACID 200 [kp_C]/1 mL; GLYCINE 200 [kp_C]/1 mL; HISTIDINE 200 [kp_C]/1 mL; LEVODOPA 200 [kp_C]/1 mL; MALVIN 200 [kp_C]/1 mL; MELANIN SYNTHETIC (TYROSINE, PEROXIDE) 200 [kp_C]/1 mL; MELATONIN 200 [kp_C]/1 mL; NITRIC OXIDE 200 [kp_C]/1 mL; NOREPINEPHRINE 200 [kp_C]/1 mL; OCTOPAMINE 200 [kp_C]/1 mL; 5-METHOXYTRYPTAMINE 200 [kp_C]/1 mL; PHENYLALANINE 200 [kp_C]/1 mL; SEROTONIN 200 [kp_C]/1 mL; TAURINE 200 [kp_C]/1 mL; TRYPTOPHAN 200 [kp_C]/1 mL; TYROSINE 200 [kp_C]/1 mL
INACTIVE INGREDIENTS: ALCOHOL; WATER

Neuro 3

Active Ingredients

5-Hydroxytryptophan 15X 200K, Acetylcholinesterase 15X 200K, Choline chloride 15X 200K, Dopamine 15X 200K, Glutamic acid 15X 200K, Glycine 15X 200K, Histidine 15X 200K, L-Dopa 15X 200K, Malvin 15X 200K, Melanin 15X 200K, Melatonin 15X 200K, Nitric oxide 15X 200K, Norepinephrine 15X 200K, Octopamine 15X 200K, O-Methyl serotonin 15X 200K, Phenylalanine 15X 200K, Serotonin 15X 200K, Taurine 15X 200K, Tryptophan 15X 200K, Tyrosine 15X 200K

Purpose:

5-Hydroxytryptophan | Stimulates serotonin
Acetylcholinesterase | Neuromuscular support
Choline chloride | Drainage
Dopamine | Neurological support
Glutamic acid | Neurological support
Glycine | Anti-aging
Histidine | Ig support
L-Dopa | Neurological support
Malvin | Neurological support
Melanin | Neurological support
Melatonin | Neurological support
Nitric oxide | Drainage
Norepinephrine | Neurological support
Octopamine | Drainage
O-Methyl serotonin | Drainage
Phenylalanine | Amino Acid Support
Serotonin | Neurological support
Taurine | Drainage
Tryptophan | Amino Acid Support
Tyrosine | Amino Acid Support

Uses

For the support & balancing of the entire neurological system

Warnings

Stop use and ask a health care practitioner if symptoms persist for more than five days or worsen. If pregnant or breastfeeding, ask a health care practitioner before use.

Dosage

1-5 spray(s); 1-3 time(s) per day or as recommended by your health care practitioner.

KEEP OUT OF REACH OF CHILDREN

Keep this and all medicines out of reach of children.

Other Ingredients

20% Alcohol and 80% Water

Other Information

Normal storage use.
Do not use if tamper-evident seal is broken or removed.

Questions

info@viatrexx.com

Principal Display Panel

ITEM: VPC0463
NDC 63776-373-15
Homeopathic remedy
Neuro 3
• For the support & balancing of the entire neurological system
Oral spray
50ml 1.7 oz
Viatrexx™ Bio Incorporated
Manufactured by Viatrexx
www.viatrexx.com
Newark, DE 19713

Neuro 3
50 mL
1.7 oz
Viatrexx™ Bio Incorporated
ITEM: VPC0463
NDC: 63776-373-15
INDICATIONS:
For the support & balancing of the entire neurological systems
DIRECTIONS:
1-5 spray(s); 1-3 time(s) per day or as recommended by your health care practitioner.
Mfg. for
Viatrexx Bio Incorporated.
www.viatrexx.com
Newark, DE 19713